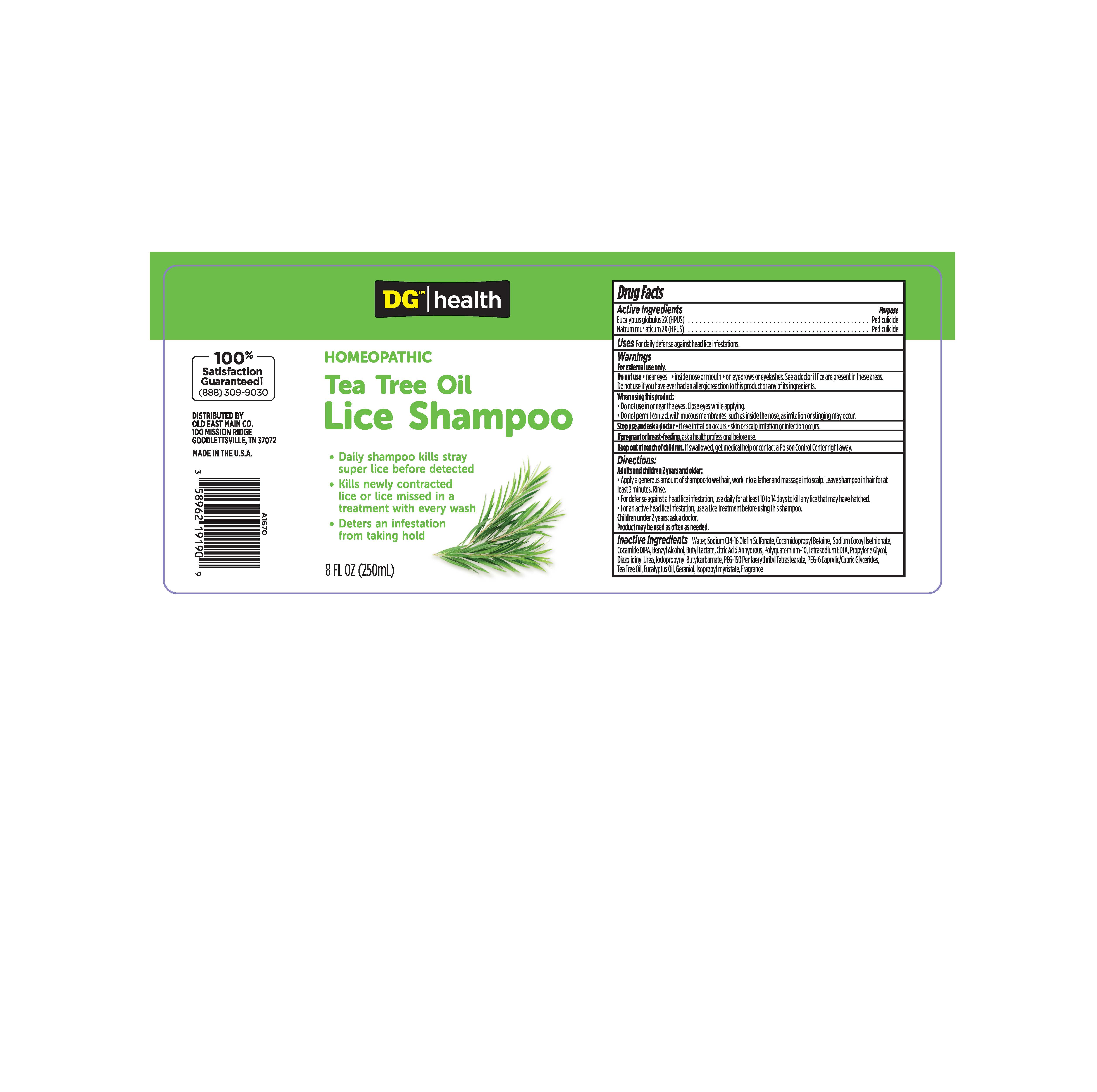 DRUG LABEL: Homeopathic Tea Tree Oil Lice
NDC: 55910-192 | Form: SHAMPOO
Manufacturer: DOLGENCORP, LLC	
Category: homeopathic | Type: HUMAN OTC DRUG LABEL
Date: 20251015

ACTIVE INGREDIENTS: EUCALYPTUS GLOBULUS LEAF 2 [hp_X]/1 mL; SODIUM CHLORIDE 2 [hp_X]/1 mL
INACTIVE INGREDIENTS: SODIUM C14-16 OLEFIN SULFONATE; COCAMIDOPROPYL BETAINE; SODIUM COCOYL ISETHIONATE; PEG-150 PENTAERYTHRITYL TETRASTEARATE; CAPRYLOCAPROYL POLYOXYLGLYCERIDES 6; COCO DIISOPROPANOLAMIDE; TEA TREE OIL; BENZYL ALCOHOL; EUCALYPTUS OIL; BUTYL LACTATE; ANHYDROUS CITRIC ACID; POLYQUATERNIUM-10 (125 MPA.S AT 2%); GERANIOL; EDETATE SODIUM; ISOPROPYL MYRISTATE; WATER; PROPYLENE GLYCOL; DIAZOLIDINYL UREA; IODOPROPYNYL BUTYLCARBAMATE

Homeopathic Tea Tree Oil Lice Shampoo

Active Ingredients

Eucalyptus globulus 2X (HPUS)

Natrum muriaticum 2X (HPUS)

Purpose

Pediculicide

Warnings

For external use only.

Do not use• near eyes • inside nose or mouth • on eyebrows or eyelashes. See a doctor if lice are present in these areas. Do not use if you have ever had an allergic reaction to this product or any of its ingredients.

When using this product:

• Do not use in or near the eyes. Close eyes while applying.

• Do not permit contact with mucous membranes, such as inside the nose, as irritation or stinging may occur.

Stop use and ask a doctor• if eye irritation occurs • skin or scalp irritation or infection occurs.

If pregnant or breast-feeding,ask a health professional before use.

Keep out of reach of children.If swallowed, get medical help or contact a Poison Control Center right away.

Directions:

Adults and children 2 years and older:

• Apply a generous amount of shampoo to wet hair, work into a lather and massage into scalp. Leave shampoo in hair for at least 3 minutes. Rinse.

• For defense against a head lice infestation, use daily for at least 10 to 14 days to kill any lice that may have hatched.

• For an active head lice infestation, use Vamousse®Lice Treatment before using this shampoo.

Children under 2 years: ask a doctor.

Product may be used as often as needed.

Inactive Ingredients

Water, Sodium C14-16 Olefin Sulfonate, Cocamidopropyl Betaine, Sodium Cocoyl Isethionate, Cocamide DIPA, Benzyl Alcohol, Butyl Lactate, Citric Acid Anhydrous, Polyquaternium-10, Tetrasodium EDTA, Propylene Glycol, Diazolidinyl Urea, Iodopropynyl Butylcarbamate, PEG-150 Pentaerythrityl Tetrastearate, PEG-6 Caprylic/Capric Glycerides, Tea Tree Oil, Eucalyptus Oil, Geraniol, Isopropyl myristate, Fragrance.

Questions?

100% Satisfaction Guaranteed!

(888)309-9030